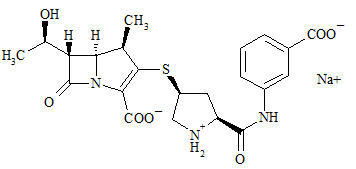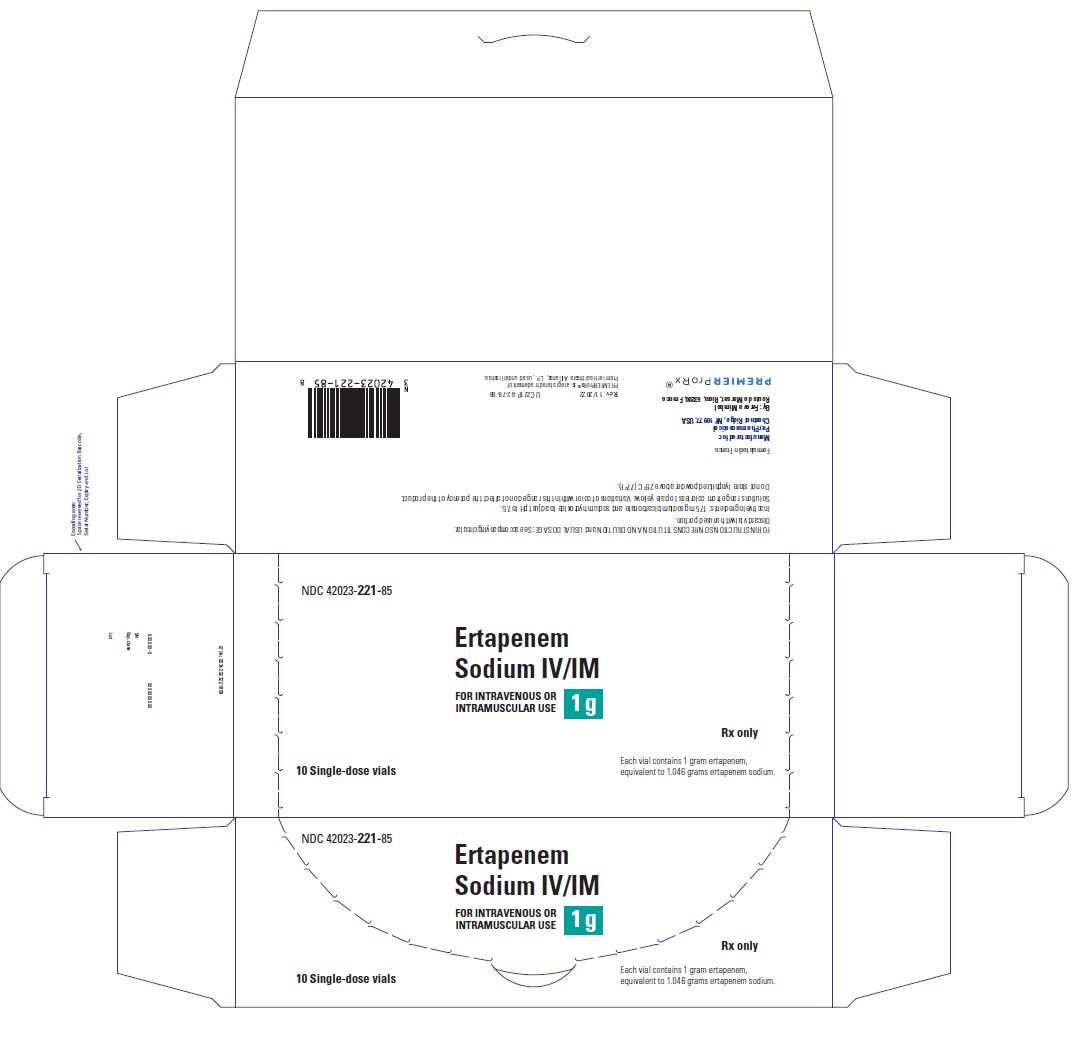 DRUG LABEL: ERTAPENEM
NDC: 42023-221 | Form: INJECTION, POWDER, LYOPHILIZED, FOR SOLUTION
Manufacturer: ENDO USA, Inc.
Category: prescription | Type: HUMAN PRESCRIPTION DRUG LABEL
Date: 20240628

ACTIVE INGREDIENTS: ERTAPENEM SODIUM 1 g/1 1
INACTIVE INGREDIENTS: sodium bicarbonate 175 mg/1 1; sodium hydroxide

HIGHLIGHTS OF PRESCRIBING INFORMATION

These highlights do not include all the information needed to use ERTAPENEM FOR INJECTION safely and effectively. See full prescribing information for ERTAPENEM FOR INJECTION.
ERTAPENEM FOR INJECTION, for intravenous or intramuscular use
Initial U.S. Approval: 2001

1 INDICATIONS AND USAGE

Ertapenem for injection is a penem antibacterial indicated in adult patients and pediatric patients (3 months of age and older) for the treatment of the following moderate to severe infections caused by susceptible bacteria:

- Complicated intra-abdominal infections. (1.1)
- Complicated skin and skin structure infections, including diabetic foot infections without osteomyelitis. (1.2)
- Community-acquired pneumonia. (1.3)
- Complicated urinary tract infections including pyelonephritis. (1.4)
- Acute pelvic infections including postpartum endomyometritis, septic abortion and post-surgical gynecologic infections. (1.5)

Ertapenem for injection is indicated in adults for the prophylaxis of surgical site infection following elective colorectal surgery. (1.6)

To reduce the development of drug-resistant bacteria and maintain the effectiveness of ertapenem for injection and other antibacterial drugs, ertapenem for injection should be used only to treat or prevent infections that are proven or strongly suspected to be caused by susceptible bacteria. (1.7)

2 DOSAGE AND ADMINISTRATION

Do not mix or co-infuse Ertapenem for injection with other medications. Do not use diluents containing dextrose (α–D–glucose). (2.1)

Ertapenem for injection should be infused over 30 minutes in both the Treatment and Prophylactic regimens. (2.1)

Dosing considerations should be made in adults with advanced or end-stage renal impairment and those on hemodialysis. (2.4, 2.5)

Treatment regimen:

- Adults and pediatric patients 13 years of age and older. The dosage should be 1 gram once a day intravenously or intramuscularly. (2.2)
- Patients 3 months to 12 years of age should be administered 15 mg/kg twice daily (not to exceed 1 g/day intravenously or intramuscularly). (2.2)
- Intravenous infusion may be administered in adults and pediatrics for up to 14 days or intramuscular injection for up to 7 days. (2.1)

Prophylaxis regimen for adults:

- 1 gram single dose given 1 hour prior to elective colorectal surgery. (2.3)

3 DOSAGE FORMS AND STRENGTHS

- For injection: Single-dose vial 1 gram. (3)

4 CONTRAINDICATIONS

- Known hypersensitivity to product components or anaphylactic reactions to β-lactams. (4)
- Due to the use of lidocaine HCl as a diluent, ertapenem for injection administered intramuscularly is contraindicated in patients with a known hypersensitivity to local anesthetics of the amide type. (4)

5 WARNINGS AND PRECAUTIONS

- Serious hypersensitivity (anaphylactic) reactions have been reported in patients receiving β-lactams. (5.1)
- Seizures and other central nervous system adverse experiences have been reported during treatment. (5.2)
- Co-administration of ertapenem for injection with valproic acid or divalproex sodium reduces the serum concentration of valproic acid potentially increasing the risk of breakthrough seizures. (5.3)
- Clostridioides difficile-associated diarrhea (ranging from mild diarrhea to fatal colitis): Evaluate if diarrhea occurs. (5.4)
- Caution should be taken when administering ertapenem for injection intramuscularly to avoid inadvertent injection into a blood vessel. (5.5)

6 ADVERSE REACTIONS

Adults:

The most common adverse reactions (≥5%) in patients treated with ertapenem for injection, including those who were switched to therapy with an oral antimicrobial, were diarrhea, nausea, headache and infused vein complication. (6.1)

In the prophylaxis indication the overall adverse experience profile was generally comparable to that observed for ertapenem in other clinical trials. (6.1)

Pediatrics:

Adverse reactions in this population were comparable to adults. The most common adverse reactions (≥5%) in pediatric patients treated with ertapenem for injection, including those who were switched to therapy with an oral antimicrobial, were diarrhea, vomiting and infusion site pain. (6.1)

To report SUSPECTED ADVERSE REACTIONS, contact Merck Sharp & Dohme LLC at 1-877-888-4231 or FDA at 1-800-FDA-1088 or www.fda.gov/medwatch .

7 DRUG INTERACTIONS

- Co-administration with probenecid inhibits the renal excretion of ertapenem and is therefore not recommended. (7.1)
- The concomitant use of ertapenem and valproic acid/divalproex sodium is generally not recommended. Anti-bacterials other than carbapenems should be considered to treat infections in patients whose seizures are well controlled on valproic acid or divalproex sodium. (5.2, 7.2)

8 USE IN SPECIFIC POPULATIONS

- Renal Impairment: Dose adjustment is necessary, if creatinine clearance is ≤30 mL/min/1.73 m^2. (2.4, 8.6, 12.3)

FULL PRESCRIBING INFORMATION

1 INDICATIONS AND USAGE

1.1 Complicated Intra-Abdominal Infections

Ertapenem for injection is indicated for the treatment of adult patients and pediatric patients (3 months of age and older) with complicated intra-abdominal infections due to Escherichia coli, Clostridium clostridioforme, Eubacterium lentum, Peptostreptococcus species, Bacteroides fragilis, Bacteroides distasonis, Bacteroides ovatus, Bacteroides thetaiotaomicron, or Bacteroides uniformis.

1.2 Complicated Skin and Skin Structure Infections, Including Diabetic Foot Infections without Osteomyelitis

Ertapenem for injection is indicated for the treatment of adult patients and pediatric patients (3 months of age and older) with complicated skin and skin structure infections, including diabetic foot infections without osteomyelitis due to Staphylococcus aureus (methicillin susceptible isolates only), Streptococcus agalactiae, Streptococcus pyogenes, Escherichia coli, Klebsiella pneumoniae, Proteus mirabilis, Bacteroides fragilis, Peptostreptococcus species, Porphyromonas asaccharolytica, or Prevotella bivia. Ertapenem for injection has not been studied in diabetic foot infections with concomitant osteomyelitis [see Clinical Studies (14)].

1.3 Community Acquired Pneumonia

Ertapenem for injection is indicated for the treatment of adult patients and pediatric patients (3 months of age and older) with community acquired pneumonia due to Streptococcus pneumoniae (penicillin susceptible isolates only) including cases with concurrent bacteremia, Haemophilus influenzae (beta-lactamase negative isolates only), or Moraxella catarrhalis.

1.4 Complicated Urinary Tract Infections Including Pyelonephritis

Ertapenem for injection is indicated for the treatment of adult patients and pediatric patients (3 months of age and older) with complicated urinary tract infections including pyelonephritis due to Escherichia coli, including cases with concurrent bacteremia, or Klebsiella pneumoniae.

1.5 Acute Pelvic Infections Including Postpartum Endomyometritis, Septic Abortion and Post-Surgical Gynecologic Infections

Ertapenem for injection is indicated for the treatment of adult patients and pediatric patients (3 months of age and older) with acute pelvic infections including postpartum endomyometritis, septic abortion and post-surgical gynecological infections due to Streptococcus agalactiae, Escherichia coli, Bacteroides fragilis, Porphyromonas asaccharolytica, Peptostreptococcus species, or Prevotella bivia.

1.6 Prophylaxis of Surgical Site Infection Following Elective Colorectal Surgery

Ertapenem for injection is indicated in adults for the prevention of surgical site infection following elective colorectal surgery.

1.7 Usage

To reduce the development of drug-resistant bacteria and maintain the effectiveness of ertapenem for injection and other antibacterial drugs, ertapenem for injection should be used only to treat or prevent infections that are proven or strongly suspected to be caused by susceptible bacteria. When culture and susceptibility information are available, they should be considered in selecting or modifying antibacterial therapy. In the absence of such data, local epidemiology and susceptibility patterns may contribute to the empiric selection of therapy.

2 DOSAGE AND ADMINISTRATION

2.1 Instructions for Use in All Patients

For Intravenous or Intramuscular Use

DO NOT MIX OR CO-INFUSE ERTAPENEM FOR INJECTION WITH OTHER MEDICATIONS. DO NOT USE DILUENTS CONTAINING DEXTROSE (α-D-GLUCOSE).

Ertapenem for injection may be administered by intravenous infusion for up to 14 days or intramuscular injection for up to 7 days. When administered intravenously, ertapenem for injection should be infused over a period of 30 minutes. Intramuscular administration of ertapenem for injection may be used as an alternative to intravenous administration in the treatment of those infections for which intramuscular therapy is appropriate.

2.2 Treatment Regimen

13 years of age and older

The dose of ertapenem for injection in patients 13 years of age and older is 1 gram (g) given once a day [see Clinical Pharmacology (12.3)].

3 months to 12 years of age

The dose of ertapenem for injection in patients 3 months to 12 years of age is 15 mg/kg twice daily (not to exceed 1 g/day).

Table 1 presents treatment guidelines for ertapenem for injection.

Table 1 Treatment Guidelines for Adults and Pediatric Patients With Normal Renal Function [defined as creatinine clearance >90 mL/min/1.73 m^2] and Body Weight
Infection [due to the designated pathogens [see Indications and Usage (1)]] | Daily Dose (IV or IM) Adults and Pediatric Patients 13 years of age and older | Daily Dose (IV or IM) Pediatric Patients 3 months to 12 years of age | Recommended Duration of Total Antimicrobial Treatment
Complicated intra-abdominal infections | 1 g | 15 mg/kg twice daily [not to exceed 1 g/day] | 5 to 14 days
Complicated skin and skin structure infections, including diabetic foot infections [Ertapenem for injection has not been studied in diabetic foot infections with concomitant osteomyelitis [see Clinical Studies (14.1)].] | 1 g | 15 mg/kg twice daily | 7 to 14 days [adult patients with diabetic foot infections received up to 28 days of treatment (parenteral or parenteral plus oral switch therapy)]
Community acquired pneumonia | 1 g | 15 mg/kg twice daily | 10 to 14 days [duration includes a possible switch to an appropriate oral therapy, after at least 3 days of parenteral therapy, once clinical improvement has been demonstrated.]
Complicated urinary tract infections, including pyelonephritis | 1 g | 15 mg/kg twice daily | 10 to 14 days
Acute pelvic infections including postpartum endomyometritis, septic abortion and post-surgical gynecologic infections | 1 g | 15 mg/kg twice daily | 3 to 10 days

2.3 Prophylactic Regimen in Adults

Table 2 presents prophylaxis guidelines for ertapenem for injection.

Table 2 Prophylaxis Guidelines for Adults
Indication | Daily Dose (IV) Adults | Recommended Duration of Total Antimicrobial Treatment
Prophylaxis of surgical site infection following elective colorectal surgery | 1 g | Single intravenous dose given 1 hour prior to surgical incision

2.4 Patients with Renal Impairment

Ertapenem for injection may be used for the treatment of infections in adult patients with renal impairment. In patients whose creatinine clearance is >30 mL/min/1.73 m^2, no dosage adjustment is necessary. Adult patients with severe renal impairment (creatinine clearance ≤30 mL/min/1.73 m^2) and end-stage renal disease (creatinine clearance ≤10 mL/min/1.73 m^2) should receive 500 mg daily. A supplementary dose of 150 mg is recommended if ertapenem is administered within 6 hours prior to hemodialysis. There are no data in pediatric patients with renal impairment.

2.5 Patients on Hemodialysis

When adult patients on hemodialysis are given the recommended daily dose of 500 mg of ertapenem for injection within 6 hours prior to hemodialysis, a supplementary dose of 150 mg is recommended following the hemodialysis session. If ertapenem for injection is given at least 6 hours prior to hemodialysis, no supplementary dose is needed. There are no data in patients undergoing peritoneal dialysis or hemofiltration. There are no data in pediatric patients on hemodialysis.

When only the serum creatinine is available, the following formula [Cockcroft and Gault equation: Cockcroft DW, Gault MH. Prediction of creatinine clearance from serum creatinine. Nephron. 1976] may be used to estimate creatinine clearance. The serum creatinine should represent a steady state of renal function.

Males: | (weight in kg) × (140-age in years)
Males: | (72) × serum creatinine (mg/100 mL)
Females: | (0.85) × (value calculated for males)

2.6 Patients with Hepatic Impairment

No dose adjustment recommendations can be made in patients with hepatic impairment [see Use in Specific Populations (8.7) and Clinical Pharmacology (12.3)].

2.7 Preparation and Reconstitution for Administration

Vials

Adults and pediatric patients 13 years of age and older

Preparation for intravenous administration:

DO NOT MIX OR CO-INFUSE ERTAPENEM FOR INJECTION WITH OTHER MEDICATIONS. DO NOT USE DILUENTS CONTAINING DEXTROSE (α-D-GLUCOSE).

ERTAPENEM FOR INJECTION MUST BE RECONSTITUTED AND THEN DILUTED PRIOR TO ADMINISTRATION.

1. Reconstitute the contents of a 1 g vial of ertapenem for injection with 10 mL of one of the following: Water for Injection, 0.9% Sodium Chloride Injection or Bacteriostatic Water for Injection, using a syringe equipped with a 21-gauge or smaller diameter needle. NOTE: Use with a needleless IV system is not recommended.
2. Shake well to dissolve and immediately transfer contents of the reconstituted vial to 50 mL of 0.9% Sodium Chloride Injection.
3. Complete the infusion within 6 hours of reconstitution.

Preparation for intramuscular administration:

ERTAPENEM FOR INJECTION MUST BE RECONSTITUTED PRIOR TO ADMINISTRATION.

1. Reconstitute the contents of a 1 g vial of ertapenem for injection with 3.2 mL of 1.0% lidocaine HCl injection [Refer to the prescribing information for lidocaine HCl.] (without epinephrine). Shake vial thoroughly to form solution.
2. Immediately withdraw the contents of the vial and administer by deep intramuscular injection into a large muscle mass (such as the gluteal muscles or lateral part of the thigh).
3. The reconstituted IM solution should be used within 1 hour after preparation. NOTE: THE RECONSTITUTED SOLUTION SHOULD NOT BE ADMINISTERED INTRAVENOUSLY.

Pediatric patients 3 months to 12 years of age

Preparation for intravenous administration:

DO NOT MIX OR CO-INFUSE ERTAPENEM FOR INJECTION WITH OTHER MEDICATIONS. DO NOT USE DILUENTS CONTAINING DEXTROSE (α-D-GLUCOSE).

ERTAPENEM FOR INJECTION MUST BE RECONSTITUTED AND THEN DILUTED PRIOR TO ADMINISTRATION.

1. Reconstitute the contents of a 1 g vial of ertapenem for injection with 10 mL of one of the following: Water for Injection, 0.9% Sodium Chloride Injection or Bacteriostatic Water for Injection, using a syringe equipped with a 21-gauge or smaller diameter needle. NOTE: Use with a needleless IV system is not recommended.
2. Shake well to dissolve and immediately withdraw a volume equal to 15 mg/kg of body weight (not to exceed 1 g/day) and dilute in 0.9% Sodium Chloride Injection to a final concentration of 20 mg/mL or less. Discard vial with unused portion of ertapenem for injection reconstituted solution.
3. Complete the infusion within 6 hours of reconstitution.

Preparation for intramuscular administration:

ERTAPENEM FOR INJECTION MUST BE RECONSTITUTED PRIOR TO ADMINISTRATION.

1. Reconstitute the contents of a 1 g vial of ertapenem for injection with 3.2 mL of 1.0% lidocaine HCl injection (without epinephrine). Shake vial thoroughly to form solution.
2. Immediately withdraw a volume equal to 15 mg/kg of body weight (not to exceed 1 g/day) and administer by deep intramuscular injection into a large muscle mass (such as the gluteal muscles or lateral part of the thigh). Discard vial with unused portion of ertapenem for injection reconstituted solution.
3. The reconstituted IM solution should be used within 1 hour after preparation. NOTE: THE RECONSTITUTED SOLUTION SHOULD NOT BE ADMINISTERED INTRAVENOUSLY.

Storage

When prepared with the diluent, ertapenem for injection maintains satisfactory potency for 6 hours at room temperature (25°C) or for 24 hours under refrigeration (5°C) and used within 4 hours after removal from refrigeration. Solutions of ertapenem for injection should not be frozen.

Before administering, see accompanying package circular for ertapenem for injection.

Parenteral drug products should be inspected visually for particulate matter and discoloration prior to use, whenever solution and container permit. Solutions of ertapenem for injection range from colorless to pale yellow. Variations of color within this range do not affect the potency of the product.

3 DOSAGE FORMS AND STRENGTHS

For Injection: Vials

Ertapenem for injection is a sterile lyophilized powder in a single-dose vial containing 1 g ertapenem equivalent to 1.046 g ertapenem sodium for intravenous infusion or for intramuscular injection after reconstitution.

4 CONTRAINDICATIONS

- Ertapenem for injection is contraindicated in patients with known hypersensitivity to any component of this product or to other drugs in the same class or in patients who have demonstrated anaphylactic reactions to beta-lactams.
- Due to the use of lidocaine HCl as a diluent, ertapenem for injection administered intramuscularly is contraindicated in patients with a known hypersensitivity to local anesthetics of the amide type.

5 WARNINGS AND PRECAUTIONS

5.1 Hypersensitivity Reactions

Serious and occasionally fatal hypersensitivity (anaphylactic) reactions have been reported in patients receiving therapy with beta-lactams. These reactions are more likely to occur in individuals with a history of sensitivity to multiple allergens. There have been reports of individuals with a history of penicillin hypersensitivity who have experienced severe hypersensitivity reactions when treated with another beta-lactam. Before initiating therapy with ertapenem for injection, careful inquiry should be made concerning previous hypersensitivity reactions to penicillins, cephalosporins, other beta-lactams and other allergens. If an allergic reaction to ertapenem for injection occurs, discontinue the drug immediately. Serious anaphylactic reactions require immediate emergency treatment as clinically indicated.

5.2 Seizure Potential

Seizures and other central nervous system (CNS) adverse experiences have been reported during treatment with ertapenem for injection [see Adverse Reactions (6.1)]. During clinical investigations in adult patients treated with ertapenem for injection (1 g once a day), seizures, irrespective of drug relationship, occurred in 0.5% of patients during study therapy plus 14-day follow-up period [see Adverse Reactions (6.1)]. These experiences have occurred most commonly in patients with CNS disorders (e.g., brain lesions or history of seizures) and/or compromised renal function. Close adherence to the recommended dosage regimen is urged, especially in patients with known factors that predispose to convulsive activity. Anticonvulsant therapy should be continued in patients with known seizure disorders. If focal tremors, myoclonus, or seizures occur, patients should be evaluated neurologically, placed on anticonvulsant therapy if not already instituted, and the dosage of ertapenem for injection re-examined to determine whether it should be decreased or discontinued.

5.3 Interaction with Valproic Acid

Case reports in the literature have shown that co-administration of carbapenems, including ertapenem, to patients receiving valproic acid or divalproex sodium results in a reduction in valproic acid concentrations. The valproic acid concentrations may drop below the therapeutic range as a result of this interaction, therefore increasing the risk of breakthrough seizures. Increasing the dose of valproic acid or divalproex sodium may not be sufficient to overcome this interaction. The concomitant use of ertapenem and valproic acid/divalproex sodium is generally not recommended. Anti-bacterials other than carbapenems should be considered to treat infections in patients whose seizures are well controlled on valproic acid or divalproex sodium. If administration of ertapenem for injection is necessary, supplemental anti-convulsant therapy should be considered [see Drug Interactions (7.2)].

5.4 Clostridioides difficile-Associated Diarrhea (CDAD)

CDAD has been reported with use of nearly all antibacterial agents, including ertapenem, and may range in severity from mild diarrhea to fatal colitis. Treatment with antibacterial agents alters the normal flora of the colon leading to overgrowth of Clostridioides difficile.

Clostridioides difficile produces toxins A and B which contribute to the development of CDAD. Hypertoxin producing strains of Clostridioides difficile cause increased morbidity and mortality, as these infections can be refractory to antimicrobial therapy and may require colectomy. CDAD must be considered in all patients who present with diarrhea following antibiotic use. Careful medical history is necessary since CDAD has been reported to occur over two months after the administration of antibacterial agents.

If CDAD is suspected or confirmed, ongoing antibiotic use not directed against Clostridioides difficile may need to be discontinued. Appropriate fluid and electrolyte management, protein supplementation, antibiotic treatment of Clostridioides difficile, and surgical evaluation should be instituted as clinically indicated.

5.5 Caution with Intramuscular Administration

Caution should be taken when administering ertapenem for injection intramuscularly to avoid inadvertent injection into a blood vessel [see Dosage and Administration (2.7)].

5.6 Development of Drug-Resistant Bacteria

As with other antibiotics, prolonged use of ertapenem for injection may result in overgrowth of non-susceptible organisms. Repeated evaluation of the patient's condition is essential. If superinfection occurs during therapy, appropriate measures should be taken.

Prescribing ertapenem for injection in the absence of a proven or strongly suspected bacterial infection or a prophylactic indication is unlikely to provide benefit to the patient and increases the risk of the development of drug-resistant bacteria.

5.7 Laboratory Tests

While ertapenem for injection possesses toxicity similar to the beta-lactam group of antibiotics, periodic assessment of organ system function, including renal, hepatic, and hematopoietic, is advisable during prolonged therapy.

6 ADVERSE REACTIONS

The following are described in greater detail in the Warnings and Precautions section.

- Hypersensitivity Reactions [see Warnings and Precautions (5.1)]
- Seizure Potential [see Warnings and Precautions (5.2)]
- Interaction with Valproic Acid [see Warnings and Precautions (5.3)]
- Clostridioides difficile-Associated Diarrhea (CDAD) [see Warnings and Precautions (5.4)]
- Caution with Intramuscular Administration [see Warnings and Precautions (5.5)]
- Development of Drug-Resistant Bacteria [see Warnings and Precautions (5.6)]
- Laboratory Tests [see Warnings and Precautions (5.7)]

6.1 Clinical Trials Experience

Because clinical trials are conducted under widely varying conditions, adverse reaction rates observed in the clinical trials of a drug cannot be directly compared to rates in the clinical trials of another drug and may not reflect the rates observed in practice.

Adults Receiving Ertapenem for Injection as a Treatment Regimen

Clinical trials enrolled 1954 patients treated with ertapenem for injection; in some of the clinical trials, parenteral therapy was followed by a switch to an appropriate oral antimicrobial [see Clinical Studies (14)]. Most adverse experiences reported in these clinical trials were described as mild to moderate in severity. Ertapenem for injection was discontinued due to adverse experiences in 4.7% of patients. Table 3 shows the incidence of adverse experiences reported in ≥2.0% of patients in these trials. The most common drug-related adverse experiences in patients treated with ertapenem for injection, including those who were switched to therapy with an oral antimicrobial, were diarrhea (5.5%), infused vein complication (3.7%), nausea (3.1%), headache (2.2%), and vaginitis in females (2.1%).

Table 3 Incidence (%) of Adverse Experiences Reported During Study Therapy Plus 14-Day Follow-Up in ≥2.0% of Adult Patients Treated With Ertapenem for injection in Clinical Trials
Adverse Events | Ertapenem for injection [Includes Phase IIb/III Complicated intra-abdominal infections, Complicated skin and skin structure infections and Acute pelvic infections trials] 1 g daily (N=802) | Piperacillin/Tazobactam 3.375 g q6h (N=774) | Ertapenem for injection [Includes Phase IIb/III Community acquired pneumonia and Complicated urinary tract infections, and Phase IIa trials] 1 g daily (N=1152) | Ceftriaxone 1 or 2 g daily (N=942)
Local:
Infused vein complication | 7.1 | 7.9 | 5.4 | 6.7
Systemic:
Death | 2.5 | 1.6 | 1.3 | 1.6
Edema/swelling | 3.4 | 2.5 | 2.9 | 3.3
Fever | 5.0 | 6.6 | 2.3 | 3.4
Abdominal pain | 3.6 | 4.8 | 4.3 | 3.9
Hypotension | 2.0 | 1.4 | 1.0 | 1.2
Constipation | 4.0 | 5.4 | 3.3 | 3.1
Diarrhea | 10.3 | 12.1 | 9.2 | 9.8
Nausea | 8.5 | 8.7 | 6.4 | 7.4
Vomiting | 3.7 | 5.3 | 4.0 | 4.0
Altered mental status [Includes agitation, confusion, disorientation, decreased mental acuity, changed mental status, somnolence, stupor] | 5.1 | 3.4 | 3.3 | 2.5
Dizziness | 2.1 | 3.0 | 1.5 | 2.1
Headache | 5.6 | 5.4 | 6.8 | 6.9
Insomnia | 3.2 | 5.2 | 3.0 | 4.1
Dyspnea | 2.6 | 1.8 | 1.0 | 2.4
Pruritus | 2.0 | 2.6 | 1.0 | 1.9
Rash | 2.5 | 3.1 | 2.3 | 1.5
Vaginitis | 1.4 | 1.0 | 3.3 | 3.7

In patients treated for complicated intra-abdominal infections, death occurred in 4.7% (15/316) of patients receiving ertapenem for injection and 2.6% (8/307) of patients receiving comparator drug. These deaths occurred in patients with significant co-morbidity and/or severe baseline infections. Deaths were considered unrelated to study drugs by investigators.

In clinical trials, seizure was reported during study therapy plus 14-day follow-up period in 0.5% of patients treated with ertapenem for injection, 0.3% of patients treated with piperacillin/tazobactam and 0% of patients treated with ceftriaxone [see Warnings and Precautions (5.2)].

Additional adverse experiences that were reported with ertapenem for injection with an incidence >0.1% within each body system are listed below

Body as a Whole: abdominal distention, pain, chills, septicemia, septic shock, dehydration, gout, malaise, asthenia/fatigue, necrosis, candidiasis, weight loss, facial edema, injection site induration, injection site pain, extravasation, phlebitis/thrombophlebitis, flank pain, syncope

Cardiovascular System: heart failure, hematoma, chest pain, hypertension, tachycardia, cardiac arrest, bradycardia, arrhythmia, atrial fibrillation, heart murmur, ventricular tachycardia, asystole, subdural hemorrhage

Digestive System: acid regurgitation, oral candidiasis, dyspepsia, gastrointestinal hemorrhage, anorexia, flatulence, C. difficile-associated diarrhea, stomatitis, dysphagia, hemorrhoids, ileus, cholelithiasis, duodenitis, esophagitis, gastritis, jaundice, mouth ulcer, pancreatitis, pyloric stenosis

Musculoskeletal System: leg pain

Nervous System & Psychiatric: anxiety, nervousness, seizure [see Warnings and Precautions (5.2)], tremor, depression, hypesthesia, spasm, paresthesia, aggressive behavior, vertigo

Respiratory System: cough, pharyngitis, rales/rhonchi, respiratory distress, pleural effusion, hypoxemia, bronchoconstriction, pharyngeal discomfort, epistaxis, pleuritic pain, asthma, hemoptysis, hiccups, voice disturbance

Skin & Skin Appendage: erythema, sweating, dermatitis, desquamation, flushing, urticaria

Special Senses: taste perversion

Urogenital System: renal impairment, oliguria/anuria, vaginal pruritus, hematuria, urinary retention, bladder dysfunction, vaginal candidiasis, vulvovaginitis.

In a clinical trial for the treatment of diabetic foot infections in which 289 adult diabetic patients were treated with ertapenem for injection, the adverse experience profile was generally similar to that seen in previous clinical trials.

Prophylaxis of Surgical Site Infection following Elective Colorectal Surgery

In a clinical trial in adults for the prophylaxis of surgical site infection following elective colorectal surgery in which 476 patients received a 1 g dose of ertapenem for injection 1 hour prior to surgery and were then followed for safety 14 days post-surgery, the overall adverse experience profile was generally comparable to that observed for ertapenem for injection in previous clinical trials. Table 4 shows the incidence of adverse experiences other than those previously described above for ertapenem for injection that were reported regardless of causality in ≥2.0% of patients in this trial.

Table 4 Incidence (%) of Adverse Experiences Reported During Study Therapy Plus 14-Day Follow-Up in ≥2.0% of Adult Patients Treated With Ertapenem for Injection for Prophylaxis of Surgical Site Infections Following Elective Colorectal Surgery
Adverse Events | Ertapenem for injection 1 g (N = 476) | Cefotetan 2 g (N = 476)
Anemia | 5.7 | 6.9
Small intestinal obstruction | 2.1 | 1.9
Pneumonia | 2.1 | 4.0
Postoperative infection | 2.3 | 4.0
Urinary tract infection | 3.8 | 5.5
Wound infection | 6.5 | 12.4
Wound complication | 2.9 | 2.3
Atelectasis | 3.4 | 1.9

Additional adverse experiences that were reported in this prophylaxis trial with ertapenem for injection, regardless of causality, with an incidence >0.5% within each body system are listed below:

Gastrointestinal Disorders: C. difficile infection or colitis, dry mouth, hematochezia

General Disorders and Administration Site Condition: crepitations

Infections and Infestations: cellulitis, abdominal abscess, fungal rash, pelvic abscess

Injury, Poisoning and Procedural Complications: incision site complication, incision site hemorrhage, intestinal stoma complication, anastomotic leak, seroma, wound dehiscence, wound secretion

Musculoskeletal and Connective Tissue Disorders: muscle spasms

Nervous System Disorders: cerebrovascular accident

Renal and Urinary Disorders: dysuria, pollakiuria

Respiratory, Thoracic and Mediastinal Disorders: crackles lung, lung infiltration, pulmonary congestion, pulmonary embolism, wheezing.

Pediatric Patients Receiving Ertapenem for Injection as a Treatment Regimen

Clinical trials enrolled 384 patients treated with ertapenem for injection; in some of the clinical trials, parenteral therapy was followed by a switch to an appropriate oral antimicrobial [see Clinical Studies (14)]. The overall adverse experience profile in pediatric patients is comparable to that in adult patients. Table 5 shows the incidence of adverse experiences reported in ≥2.0% of pediatric patients in clinical trials. The most common drug-related adverse experiences in pediatric patients treated with ertapenem for injection, including those who were switched to therapy with an oral antimicrobial, were diarrhea (6.5%), infusion site pain (5.5%), infusion site erythema (2.6%), vomiting (2.1%).

Table 5 Incidence (%) of Adverse Experiences Reported During Study Therapy Plus 14-Day Follow-Up in ≥2.0% of Pediatric Patients Treated With Ertapenem for injection in Clinical Trials
Adverse Events | Ertapenem for injection [Includes Phase IIb Complicated skin and skin structure infections, Community acquired pneumonia and Complicated urinary tract infections trials in which patients 3 months to 12 years of age received ertapenem for injection 15 mg/kg IV twice daily up to a maximum of 1 g or ceftriaxone 50 mg/kg/day IV in two divided doses up to a maximum of 2 g, and patients 13 to 17 years of age received ertapenem for injection 1 g IV daily or ceftriaxone 50 mg/kg/day IV in a single daily dose.] , [Includes Phase IIb Acute pelvic infections and Complicated intra-abdominal infections trials in which patients 3 months to 12 years of age received ertapenem for injection 15 mg/kg IV twice daily up to a maximum of 1 g and patients 13 to 17 years of age received ertapenem for injection 1 g IV daily or ticarcillin/clavulanate 50 mg/kg for patients <60 kg or ticarcillin/clavulanate 3.0 g for patients >60 kg, 4 or 6 times a day.] (N=384) | Ceftriaxone (N=100) | Ticarcillin/Clavulanate (N=24)
Local:
Infusion Site Erythema | 3.9 | 3.0 | 8.3
Infusion Site Pain | 7.0 | 4.0 | 20.8
Systemic:
Abdominal Pain | 4.7 | 3.0 | 4.2
Constipation | 2.3 | 0.0 | 0.0
Diarrhea | 11.7 | 17.0 | 4.2
Loose Stools | 2.1 | 0.0 | 0.0
Vomiting | 10.2 | 11.0 | 8.3
Pyrexia | 4.9 | 6.0 | 8.3
Upper Respiratory Tract Infection | 2.3 | 3.0 | 0.0
Headache | 4.4 | 4.0 | 0.0
Cough | 4.4 | 3.0 | 0.0
Diaper Dermatitis | 4.7 | 4.0 | 0.0
Rash | 2.9 | 2.0 | 8.3

Additional adverse experiences that were reported with ertapenem for injection with an incidence >0.5% within each body system are listed below:

Gastrointestinal Disorders: nausea

General Disorders and Administration Site Condition: hypothermia, chest pain, upper abdominal pain; infusion site pruritus, induration, phlebitis, swelling, and warmth

Infections and Infestations: candidiasis, oral candidiasis, viral pharyngitis, herpes simplex, ear infection, abdominal abscess

Metabolism and Nutrition Disorders: decreased appetite

Musculoskeletal and Connective Tissue Disorders: arthralgia

Nervous System Disorders: dizziness, somnolence

Psychiatric Disorders: insomnia

Reproductive System and Breast Disorders: genital rash

Respiratory, Thoracic and Mediastinal Disorders: wheezing, nasopharyngitis, pleural effusion, rhinitis, rhinorrhea

Skin and Subcutaneous Tissue Disorders: dermatitis, pruritus, rash erythematous, skin lesion

Vascular Disorders: phlebitis.

6.2 Post-Marketing Experience

The following additional adverse reactions have been identified during the post-approval use of ertapenem for injection. Because these reactions are reported voluntarily from a population of uncertain size, it is not always possible to reliably estimate their frequency or establish a causal relationship to drug exposure.

Gastrointestinal Disorders: teeth staining

Immune System Disorders: anaphylaxis including anaphylactoid reactions

Musculoskeletal and Connective Tissue Disorders: muscular weakness

Nervous System Disorders: coordination abnormal, depressed level of consciousness, dyskinesia, gait disturbance, myoclonus, tremor, encephalopathy (recovery was prolonged in patients with renal impairment)

Psychiatric Disorders: altered mental status (including aggression, delirium), hallucinations

Skin and Subcutaneous Tissue Disorders: Acute Generalized Exanthematous Pustulosis (AGEP), Drug Reaction with Eosinophilia and Systemic Symptoms (DRESS syndrome), hypersensitivity vasculitis

6.3 Adverse Laboratory Changes in Clinical Trials

Adults Receiving Ertapenem for Injection as Treatment Regimen

Laboratory adverse experiences that were reported during therapy in ≥2.0% of adult patients treated with ertapenem for injection in clinical trials are presented in Table 6. Drug-related laboratory adverse experiences that were reported during therapy in ≥2.0% of adult patients treated with ertapenem for injection, including those who were switched to therapy with an oral antimicrobial, in clinical trials were ALT increased (6.0%), AST increased (5.2%), serum alkaline phosphatase increased (3.4%), and platelet count increased (2.8%). Ertapenem for injection was discontinued due to laboratory adverse experiences in 0.3% of patients.

Table 6 Incidence [Number of patients with laboratory adverse experiences/Number of patients with the laboratory test] (%) of Laboratory Adverse Experiences Reported During Study Therapy Plus 14-Day Follow-Up in ≥2.0% of Adult Patients Treated With Ertapenem for injection in Clinical Trials
Adverse laboratory experiences | Ertapenem for injection [Includes Phase IIb/III Complicated intra-abdominal infections, Complicated skin and skin structure infections and Acute pelvic infections trials] 1 g daily (n [Number of patients with one or more laboratory tests] =766) | Piperacillin/Tazobactam 3.375 g q6h (n=755) | Ertapenem for injection [Includes Phase IIb/III Community acquired pneumonia and Complicated urinary tract infections, and Phase IIa trials] 1 g daily (n=1122) | Ceftriaxone 1 or 2 g daily (n=920)
ALT increased | 8.8 | 7.3 | 8.3 | 6.9
AST increased | 8.4 | 8.3 | 7.1 | 6.5
Serum alkaline phosphatase increased | 6.6 | 7.2 | 4.3 | 2.8
Eosinophils increased | 1.1 | 1.1 | 2.1 | 1.8
Hematocrit decreased | 3.0 | 2.9 | 3.4 | 2.4
Hemoglobin decreased | 4.9 | 4.7 | 4.5 | 3.5
Platelet count increased | 6.5 | 6.3 | 4.3 | 3.5
Urine RBCs increased | 2.5 | 2.9 | 1.1 | 1.0
Urine WBCs increased | 2.5 | 3.2 | 1.6 | 1.1

Additional laboratory adverse experiences that were reported during therapy in >0.1% of patients treated with ertapenem for injection in clinical trials include: increases in serum creatinine, serum glucose, BUN, total, direct and indirect serum bilirubin, serum sodium and potassium, PT and PTT; decreases in serum potassium, serum albumin, WBC, platelet count, and segmented neutrophils.

In a clinical trial for the treatment of diabetic foot infections in which 289 adult diabetic patients were treated with ertapenem for injection, the laboratory adverse experience profile was generally similar to that seen in previous clinical trials.

Prophylaxis of Surgical Site Infection following Elective Colorectal Surgery

In a clinical trial in adults for the prophylaxis of surgical site infection following elective colorectal surgery in which 476 patients received a 1 g dose of ertapenem for injection 1 hour prior to surgery and were then followed for safety 14 days post-surgery, the overall laboratory adverse experience profile was generally comparable to that observed for ertapenem for injection in previous clinical trials.

Pediatric Patients Receiving Ertapenem for Injection as a Treatment Regimen

Laboratory adverse experiences that were reported during therapy in ≥2.0% of pediatric patients treated with ertapenem for injection in clinical trials are presented in Table 7. Drug-related laboratory adverse experiences that were reported during therapy in ≥2.0% of pediatric patients treated with ertapenem for injection, including those who were switched to therapy with an oral antimicrobial, in clinical trials were neutrophil count decreased (3.0%), ALT increased (2.2%), and AST increased (2.1%).

Table 7 Incidence [Number of patients with laboratory adverse experiences/Number of patients with the laboratory test; where at least 300 patients had the test] (%) of Specific Laboratory Adverse Experiences Reported During Study Therapy Plus 14-Day Follow-Up in ≥2.0% of Pediatric Patients Treated With Ertapenem for injection in Clinical Trials
Adverse laboratory experiences | Ertapenem for injection (n [Number of patients with one or more laboratory tests] =379) | Ceftriaxone (n=97) | Ticarcillin/Clavulanate (n=24)
ALT Increased | 3.8 | 1.1 | 4.3
AST Increased | 3.8 | 1.1 | 4.3
Neutrophil Count Decreased | 5.8 | 3.1 | 0.0

Additional laboratory adverse experiences that were reported during therapy in >0.5% of patients treated with ertapenem for injection in clinical trials include: alkaline phosphatase increased, eosinophil count increased, platelet count increased, white blood cell count decreased and urine protein present.

7 DRUG INTERACTIONS

7.1 Probenecid

Probenecid interferes with the active tubular secretion of ertapenem, resulting in increased plasma concentrations of ertapenem [see Clinical Pharmacology (12.3)]. Co-administration of probenecid with ertapenem is not recommended.

7.2 Valproic Acid

Case reports in the literature have shown that co-administration of carbapenems, including ertapenem, to patients receiving valproic acid or divalproex sodium results in a reduction of valproic acid concentrations. The valproic acid concentrations may drop below the therapeutic range as a result of this interaction, therefore increasing the risk of breakthrough seizures. Although the mechanism of this interaction is unknown, data from in vitro and animal studies suggest that carbapenems may inhibit the hydrolysis of valproic acid's glucuronide metabolite (VPA-g) back to valproic acid, thus decreasing the serum concentrations of valproic acid [see Warnings and Precautions (5.3)].

8 USE IN SPECIFIC POPULATIONS

8.1 Pregnancy

Risk Summary

Available data from a small number of post-marketing cases with ertapenem for injection use in pregnancy are insufficient to inform any drug-associated risks for major birth defects, miscarriage, or adverse maternal or fetal outcomes. In animal reproduction studies after intravenous administration of ertapenem during the period of organogenesis, there was no evidence of developmental malformations in rats at systemic exposures (AUC) up to approximately 1.2 times the human exposure at the maximum recommended human dose (MRHD) and in mice at doses up to approximately 3 times the MRHD based on body surface area comparison. In pregnant rats administered ertapenem during organogenesis through lactation, fetal toxicity, developmental delays, and impaired reproduction did not occur in first generation offspring at systemic exposures (AUC) approximately 1.2 times the human exposure at the MRHD (see Data).

The estimated background risk of major birth defects and miscarriage for the indicated population is unknown. All pregnancies have a background risk of birth defect, loss, or other adverse outcomes. In the U.S. general population, the estimated background risk of major birth defects and miscarriage in clinically recognized pregnancies is 2 to 4% and 15 to 20%, respectively.

Data

Animal Data

In pregnant rats, intravenous administration of ertapenem dosages of up to 700 mg/kg/day (approximately 1.2 times the MRHD based on AUC) during the period of organogenesis (gestation days [GD] 6-20) revealed no maternal or embryofetal effects.

Pregnant mice intravenously administered ertapenem dosages of up to 700 mg/kg/day (approximately 3 times the MRHD based on body surface area comparison) during the period of organogenesis (GD 6-15) showed slight decreases in average fetal weight and an associated decrease in the average number of ossified sacrocaudal vertebrae. There were no maternal effects at any dosage.

In a pre-postnatal study in rats, ertapenem administered to pregnant rats at dosages up to 700 mg/kg/day (approximately 1.2 times the MRHD based on AUC) during organogenesis through lactation, (GD 6 until Lactation Day (LD) 20) did not result in fetal toxicity, developmental delays, or impaired reproduction in first generation offspring, and fetal deaths and malformations were not increased in second generation offspring.

8.2 Lactation

Risk Summary

Ertapenem is present in human milk (see Data). There are no data on the effects on the breastfed infant or the effects on milk production. The developmental and health benefits of breastfeeding should be considered along with the mother's clinical need for ertapenem for injection and any potential adverse effects on the breastfed infant from ertapenem for injection or from the underlying maternal condition.

Data

The concentration of ertapenem in breast milk from 5 lactating women with pelvic infections (5 to 14 days postpartum) measured at random time points daily for 5 consecutive days following the last 1 g dose of intravenous therapy (3 to 10 days of therapy) showed low levels. The concentration of ertapenem in breast milk within 24 hours of the last dose of therapy in all 5 women ranged from (<0.13 (lower limit of quantitation) to 0.38 mcg/mL), although peak concentrations were not assessed. By day 5 after discontinuation of therapy, the level of ertapenem was undetectable in the breast milk of 4 women and below the lower limit of quantitation (<0.13 mcg/mL) in 1 woman. The concentration of ertapenem in transitional milk observed in this study may not reflect the concentration of ertapenem in mature milk.

8.4 Pediatric Use

Safety and effectiveness of ertapenem for injection in pediatric patients 3 months to 17 years of age are supported by evidence from adequate and well-controlled trials in adults, pharmacokinetic data in pediatric patients, and additional data from comparator-controlled trials in pediatric patients 3 months to 17 years of age [see Indications and Usage (1.1), (1.2), (1.3), (1.4) and (1.5) and Clinical Studies (14.2)].

Ertapenem for injection is not recommended in infants under 3 months of age as no data are available.

Ertapenem for injection is not recommended in the treatment of meningitis in the pediatric population due to lack of sufficient CSF penetration.

8.5 Geriatric Use

Of the 1,835 patients in Phase 2b/3 trials treated with ertapenem for injection, approximately 26 percent were 65 and over, while approximately 12 percent were 75 and over. No overall differences in safety or effectiveness were observed between these patients and younger patients. Other reported clinical experience has not identified differences in responses between the elderly and younger patients, but greater sensitivity of some older individuals cannot be ruled out.

This drug is known to be substantially excreted by the kidney, and the risk of toxic reactions to this drug may be greater in patients with impaired renal function. Because elderly patients are more likely to have decreased renal function, care should be taken in dose selection, and it may be useful to monitor renal function [see Dosage and Administration (2.2)].

8.6 Patients with Renal Impairment

Dosage adjustment is necessary in patients with creatinine clearance 30 mL/min or less [see Dosage and Administration (2.4) and Clinical Pharmacology (12.3)].

8.7 Patients with Hepatic Impairment

The pharmacokinetics of ertapenem in patients with hepatic impairment have not been established. Of the total number of patients in clinical trials, 37 patients receiving ertapenem 1 g daily and 36 patients receiving comparator drugs were considered to have Child-Pugh Class A, B, or C liver impairment. The incidence of adverse experiences in patients with hepatic impairment was similar between the ertapenem group and the comparator groups.

10 OVERDOSAGE

No specific information is available on the treatment of overdosage with ertapenem for injection. Intentional overdosing of ertapenem for injection is unlikely. Intravenous administration of ertapenem for injection at a dose of 2 g over 30 min or 3 g over 1-2h in healthy adult volunteers resulted in an increased incidence of nausea. In clinical trials in adults, inadvertent administration of three 1 g doses of ertapenem for injection in a 24 hour period resulted in diarrhea and transient dizziness in one patient. In pediatric clinical trials, a single intravenous dose of 40 mg/kg up to a maximum of 2 g did not result in toxicity.

In the event of an overdose, ertapenem for injection should be discontinued and general supportive treatment given until renal elimination takes place.

Ertapenem for injection can be removed by hemodialysis; the plasma clearance of the total fraction of ertapenem was increased 30% in subjects with end-stage renal disease when hemodialysis (4 hour session) was performed immediately following administration. However, no information is available on the use of hemodialysis to treat overdosage.

11 DESCRIPTION

Ertapenem for injection is a sterile, synthetic, parenteral, 1-β methyl-carbapenem that is structurally related to beta-lactam antibiotics.

Chemically, ertapenem for injection is described as [4R-[3(3S*,5S*),4α,5β,6β(R*)]]-3-[[5-[[(3-carboxyphenyl)amino]carbonyl]-3-pyrrolidinyl]thio]-6-(1-hydroxyethyl)-4-methyl-7-oxo-1-azabicyclo[3.2.0]hept-2-ene-2-carboxylic acid monosodium salt. Its molecular weight is 497.50. The empirical formula is C22H24N3O7SNa, and its structural formula is:

Ertapenem sodium is a white to off-white hygroscopic, weakly crystalline powder. It is soluble in water and 0.9% sodium chloride solution, practically insoluble in ethanol, and insoluble in isopropyl acetate and tetrahydrofuran.

Ertapenem for injection is supplied as sterile lyophilized powder for intravenous infusion after reconstitution with appropriate diluent [see Dosage and Administration (2.7)] and transfer to 50 mL 0.9% Sodium Chloride Injection or for intramuscular injection following reconstitution with 1% lidocaine hydrochloride. Each single-dose vial contains 1 gram ertapenem equivalent to 1.046 grams ertapenem sodium. The sodium content is approximately 137 mg (approximately 6.0 mEq).

Each vial of ertapenem for injection contains the following inactive ingredients: 175 mg sodium bicarbonate and sodium hydroxide to adjust pH to 7.5.

12 CLINICAL PHARMACOLOGY

12.1 Mechanism of Action

Ertapenem sodium is a carbapenem antibiotic [see Clinical Pharmacology (12.4)].

12.3 Pharmacokinetics

Average plasma concentrations (mcg/mL) of ertapenem following a single 30-minute infusion of a 1 g intravenous (IV) dose and administration of a single 1 g intramuscular (IM) dose in healthy young adults are presented in Table 8.

Table 8 Plasma Concentrations of Ertapenem in Adults After Single Dose Administration
 |  |  | Average Plasma Concentrations (mcg/mL)
Dose/Route | 0.5 hr | 1 hr | 2 hr | 4 hr | 6 hr | 8 hr | 12 hr | 18 hr | 24 hr
1 g IV [Infused at a constant rate over 30 minutes] | 155 | 115 | 83 | 48 | 31 | 20 | 9 | 3 | 1
1 g IM | 33 | 53 | 67 | 57 | 40 | 27 | 13 | 4 | 2

The area under the plasma concentration-time curve (AUC) of ertapenem in adults increased less-than dose-proportional based on total ertapenem concentrations over the 0.5 to 2 g dose range, whereas the AUC increased greater-than dose-proportional based on unbound ertapenem concentrations. Ertapenem exhibits non-linear pharmacokinetics due to concentration-dependent plasma protein binding at the proposed therapeutic dose [see Clinical Pharmacology (12.3)]. There is no accumulation of ertapenem following multiple IV or IM 1 g daily doses in healthy adults.

Average plasma concentrations (mcg/mL) of ertapenem in pediatric patients are presented in Table 9.

Table 9 Plasma Concentrations of Ertapenem in Pediatric Patients After Single IV [Infused at a constant rate over 30 minutes] Dose Administration
Age Group | Dose | Average Plasma Concentrations (mcg/mL)
 |  | 0.5 hr | 1 hr | 2 hr | 4 hr | 6 hr | 8 hr | 12 hr | 24 hr
3 to 23 months
 | 15 mg/kg [up to a maximum dose of 1 g/day] | 103.8 | 57.3 | 43.6 | 23.7 | 13.5 | 8.2 | 2.5 | -
 | 20 mg/kg | 126.8 | 87.6 | 58.7 | 28.4 | - | 12.0 | 3.4 | 0.4
 | 40 mg/kg [up to a maximum dose of 2 g/day] | 199.1 | 144.1 | 95.7 | 58.0 | - | 20.2 | 7.7 | 0.6
2 to 12 years
 | 15 mg/kg | 113.2 | 63.9 | 42.1 | 21.9 | 12.8 | 7.6 | 3.0 | -
 | 20 mg/kg | 147.6 | 97.6 | 63.2 | 34.5 | - | 12.3 | 4.9 | 0.5
 | 40 mg/kg | 241.7 | 152.7 | 96.3 | 55.6 | - | 18.8 | 7.2 | 0.6
13 to 17 years
 | 20 mg/kg | 170.4 | 98.3 | 67.8 | 40.4 | - | 16.0 | 7.0 | 1.1
 | 1 g [Based on three patients receiving 1 g ertapenem who volunteered for pharmacokinetic assessment in one of the two safety and efficacy trials] | 155.9 | 110.9 | 74.8 | - | 24.0 | - | 6.2 | -
 | 40 mg/kg | 255.0 | 188.7 | 127.9 | 76.2 | - | 31.0 | 15.3 | 2.1

Absorption

Ertapenem, reconstituted with 1% lidocaine HCl injection, USP (in saline without epinephrine), is almost completely absorbed following intramuscular (IM) administration at the recommended dose of 1 g. The mean bioavailability is approximately 90%. Following 1 g daily IM administration, mean peak plasma concentrations (Cmax) are achieved in approximately 2.3 hours (Tmax).

Distribution

Ertapenem is highly bound to human plasma proteins, primarily albumin. In healthy young adults, the protein binding of ertapenem decreases as plasma concentrations increase, from approximately 95% bound at an approximate plasma concentration of <100 micrograms (mcg)/mL to approximately 85% bound at an approximate plasma concentration of 300 mcg/mL.

The apparent volume of distribution at steady state (Vss) of ertapenem in adults is approximately 0.12 liter/kg, approximately 0.2 liter/kg in pediatric patients 3 months to 12 years of age and approximately 0.16 liter/kg in pediatric patients 13 to 17 years of age.

The concentrations of ertapenem achieved in suction-induced skin blister fluid at each sampling point on the third day of 1 g once daily IV doses are presented in Table 10. The ratio of AUC0-24 in skin blister fluid/AUC0-24 in plasma is 0.61.

Table 10 Concentrations (mcg/mL) of Ertapenem in Adult Skin Blister Fluid at each Sampling Point on the Third Day of 1-g Once Daily IV Doses
0.5 hr | 1 hr | 2 hr | 4 hr | 8 hr | 12 hr | 24 hr
7 | 12 | 17 | 24 | 24 | 21 | 8

Metabolism

In healthy young adults, after infusion of 1 g IV radiolabeled ertapenem, the plasma radioactivity consists predominantly (94%) of ertapenem. The major metabolite of ertapenem is the inactive ring-opened derivative formed by hydrolysis of the beta-lactam ring.

Elimination

Ertapenem is eliminated primarily by the kidneys. The mean plasma half-life in healthy young adults is approximately 4 hours and the plasma clearance is approximately 1.8 L/hour. The mean plasma half-life in pediatric patients 13 to 17 years of age is approximately 4 hours and approximately 2.5 hours in pediatric patients 3 months to 12 years of age.

Following the administration of 1 g IV radiolabeled ertapenem to healthy young adults, approximately 80% is recovered in urine and 10% in feces. Of the 80% recovered in urine, approximately 38% is excreted as unchanged drug and approximately 37% as the ring-opened metabolite.

In healthy young adults given a 1 g IV dose, the mean percentage of the administered dose excreted in urine was 17.4% during 0-2 hours postdose, 5.4% during 4-6 hours postdose, and 2.4% during 12-24 hours postdose.

Special Populations

Renal Impairment

Total and unbound fractions of ertapenem pharmacokinetics were investigated in 26 adult subjects (31 to 80 years of age) with varying degrees of renal impairment. Following a single 1 g IV dose of ertapenem, the unbound AUC increased 1.5-fold and 2.3-fold in subjects with mild renal impairment (CLCR 60-90 mL/min/1.73 m^2) and moderate renal impairment (CLCR 31-59 mL/min/1.73 m^2), respectively, compared with healthy young subjects (25 to 45 years of age). No dosage adjustment is necessary in patients with CLCR ≥31 mL/min/1.73 m^2. The unbound AUC increased 4.4-fold and 7.6-fold in subjects with advanced renal impairment (CLCR 5-30 mL/min/1.73 m^2) and end-stage renal disease (CLCR <10 mL/min/1.73 m^2), respectively, compared with healthy young subjects. The effects of renal impairment on AUC of total drug were of smaller magnitude. The recommended dose of ertapenem in adult patients with CLCR ≤30 mL/min/1.73 m^2 is 0.5 grams every 24 hours. Following a single 1 g IV dose given immediately prior to a 4 hour hemodialysis session in 5 adult patients with end-stage renal disease, approximately 30% of the dose was recovered in the dialysate. Dose adjustments are recommended for patients with severe renal impairment and end-stage renal disease [see Dosage and Administration (2.4)]. There are no data in pediatric patients with renal impairment.

Hepatic Impairment

The pharmacokinetics of ertapenem in patients with hepatic impairment have not been established. However, ertapenem does not appear to undergo hepatic metabolism based on in vitro studies and approximately 10% of an administered dose is recovered in the feces [see Clinical Pharmacology (12.3) and Dosage and Administration (2.6)].

Gender

The effect of gender on the pharmacokinetics of ertapenem was evaluated in healthy male (n=8) and healthy female (n=8) subjects. The differences observed could be attributed to body size when body weight was taken into consideration. No dose adjustment is recommended based on gender.

Geriatric Patients

The impact of age on the pharmacokinetics of ertapenem was evaluated in healthy male (n=7) and healthy female (n=7) subjects ≥65 years of age. The total and unbound AUC increased 37% and 67%, respectively, in elderly adults relative to young adults. These changes were attributed to age-related changes in creatinine clearance. No dosage adjustment is necessary for elderly patients with normal (for their age) renal function.

Pediatric Patients

Plasma concentrations of ertapenem are comparable in pediatric patients 13 to 17 years of age and adults following a 1 g once daily IV dose.

Following the 20 mg/kg dose (up to a maximum dose of 1 g), the pharmacokinetic parameter values in patients 13 to 17 years of age (N=6) were generally comparable to those in healthy young adults.

Plasma concentrations at the midpoint of the dosing interval following a single 15 mg/kg IV dose of ertapenem in patients 3 months to 12 years of age are comparable to plasma concentrations at the midpoint of the dosing interval following a 1 g once daily IV dose in adults [see Clinical Pharmacology (12.3)]. The plasma clearance (mL/min/kg) of ertapenem in patients 3 months to 12 years of age is approximately 2-fold higher as compared to that in adults. At the 15 mg/kg dose, the AUC value (doubled to model a twice daily dosing regimen, i.e., 30 mg/kg/day exposure) in patients 3 months to 12 years of age was comparable to the AUC value in young healthy adults receiving a 1 g IV dose of ertapenem.

Drug Interactions

When ertapenem is co-administered with probenecid (500 mg p.o. every 6 hours), probenecid competes for active tubular secretion and reduces the renal clearance of ertapenem. Based on total ertapenem concentrations, probenecid increased the AUC of ertapenem by 25%, and reduced the plasma and renal clearance of ertapenem by 20% and 35%, respectively. The half-life of ertapenem was increased from 4.0 to 4.8 hours.

In vitro studies in human liver microsomes indicate that ertapenem does not inhibit metabolism mediated by any of the following cytochrome p450 (CYP) isoforms: 1A2, 2C9, 2C19, 2D6, 2E1 and 3A4.

In vitro studies indicate that ertapenem does not inhibit P-glycoprotein-mediated transport of digoxin or vinblastine and that ertapenem is not a substrate for P-glycoprotein-mediated transport.

12.4 Microbiology

Mechanism of Action

Ertapenem has in vitro activity against Gram-positive and Gram-negative aerobic and anaerobic bacteria. The bactericidal activity of ertapenem results from the inhibition of cell wall synthesis and is mediated through ertapenem binding to penicillin binding proteins (PBPs). In Escherichia coli, it has strong affinity toward PBPs 1a, 1b, 2, 3, 4 and 5 with preference for PBPs 2 and 3.

Resistance

Ertapenem is stable against hydrolysis by a variety of beta-lactamases, including penicillinases, and cephalosporinases and extended spectrum beta-lactamases. Ertapenem is hydrolyzed by metallo-beta-lactamases.

Antimicrobial Activity

Ertapenem has been shown to be active against most isolates of the following microorganisms both in vitro and in clinical infections as described in the INDICATIONS AND USAGE section:

Gram-positive bacteria:
Staphylococcus aureus (methicillin susceptible isolates only)
Streptococcus agalactiae
Streptococcus pneumoniae (penicillin susceptible isolates only)
Streptococcus pyogenes

Gram-negative bacteria:

Escherichia coli
Haemophilus influenzae (beta-lactamase negative isolates only)
Klebsiella pneumoniae
Moraxella catarrhalis
Proteus mirabilis

Anaerobic bacteria:

Bacteroides fragilis
Bacteroides distasonis
Bacteroides ovatus
Bacteroides thetaiotaomicron
Bacteroides uniformis
Clostridium clostridioforme
Eubacterium lentum
Peptostreptococcus species
Porphyromonas asaccharolytica
Prevotella bivia

The following in vitro data are available, but their clinical significance is unknown. At least 90% of the following bacteria exhibit an in vitro minimum inhibitory concentration (MIC) less than or equal to the susceptible breakpoint for ertapenem. However, the efficacy of ertapenem in treating clinical infections due to these bacteria has not been established in adequate and well-controlled clinical trials:

Gram-positive bacteria:

Staphylococcus epidermidis (methicillin susceptible isolates only)
Streptococcus pneumoniae (penicillin-intermediate isolates)

Gram-negative bacteria:

Citrobacter freundii
Citrobacter koseri
Enterobacter aerogenes
Enterobacter cloacae
Haemophilus influenzae (beta-lactamase positive isolates only)
Haemophilus parainfluenzae
Klebsiella oxytoca (excluding ESBL producing isolates)
Morganella morganii
Proteus vulgaris
Providencia rettgeri
Providencia stuartii
Serratia marcescens

Anaerobic bacteria:

Bacteroides vulgatus
Clostridium perfringens
Fusobacterium spp.

Susceptibility Testing

For specific information regarding susceptibility testing methods, interpretive criteria, and associated test methods and quality control standards recognized by FDA for ertapenem, please see: https://www.fda.gov/STIC.

13 NONCLINICAL TOXICOLOGY

13.1 Carcinogenesis, Mutagenesis, Impairment of Fertility

Carcinogenesis and Mutagenesis

No long-term studies in animals have been performed to evaluate the carcinogenic potential of ertapenem.

Ertapenem was not genotoxic in in vitro or in vivo assays, including: an alkaline elution/rat hepatocyte assay, a chromosomal aberration assay in Chinese hamster ovary cells, a TK6 human lymphoblastoid cell mutagenesis assay and a mouse micronucleus assay.

Impairment of Fertility

In rats, intravenous dosages up to 700 mg/kg/day (approximately 1.2 times the human exposure at the recommended human dose of 1 g based on plasma AUC) did not impair fertility.

13.2 Animal Toxicology and/or Pharmacology

In repeat-dose studies in rats, treatment-related neutropenia occurred at every dose-level tested, including the lowest dose of 2 mg/kg (approximately 2% of the human dose on a body surface area basis).

Studies in rabbits and Rhesus monkeys were inconclusive with regard to the effect on neutrophil counts.

14 CLINICAL STUDIES

14.1 Adults

Complicated Intra-Abdominal Infections

Ertapenem was evaluated in adults for the treatment of complicated intra-abdominal infections in a randomized, double-blind, non-inferiority clinical trial. This trial compared ertapenem (1 g intravenously once a day) with piperacillin/tazobactam (3.375 g intravenously every 6 hours) for 5 to 14 days and enrolled 665 patients with localized complicated appendicitis, and any other complicated intra-abdominal infection including colonic, small intestinal, and biliary infections and generalized peritonitis. The combined clinical and microbiologic success rates in the microbiologically evaluable population at 4 to 6 weeks posttherapy (test-of-cure) were 83.6% (163/195) for ertapenem and 80.4% (152/189) for piperacillin/tazobactam.

Complicated Skin and Skin Structure Infections

Ertapenem was evaluated in adults for the treatment of complicated skin and skin structure infections in a randomized, double-blind, non-inferiority clinical trial. This trial compared ertapenem (1 g intravenously once a day) with piperacillin/tazobactam (3.375 g intravenously every 6 hours) for 7 to 14 days and enrolled 540 patients including patients with deep soft tissue abscess, posttraumatic wound infection and cellulitis with purulent drainage. The clinical success rates at 10 to 21 days posttherapy (test-of-cure) were 83.9% (141/168) for ertapenem and 85.3% (145/170) for piperacillin/tazobactam.

Diabetic Foot Infections

Ertapenem was evaluated in adults for the treatment of diabetic foot infections without concomitant osteomyelitis in a multicenter, randomized, double-blind, non-inferiority clinical trial. This trial compared ertapenem (1 g intravenously once a day) with piperacillin/tazobactam (3.375 g intravenously every 6 hours). Test-of-cure was defined as clinical response between treatment groups in the clinically evaluable population at the 10-day posttherapy follow-up visit. The trial included 295 patients randomized to ertapenem and 291 patients to piperacillin/tazobactam. Both regimens allowed the option to switch to oral amoxicillin/clavulanate for a total of 5 to 28 days of treatment (parenteral and oral). All patients were eligible to receive appropriate adjunctive treatment methods, such as debridement, as is typically required in the treatment of diabetic foot infections, and most patients received these treatments. Patients with suspected osteomyelitis could be enrolled if all the infected bone was removed within 2 days of initiation of study therapy, and preferably within the prestudy period. Investigators had the option to add open-label vancomycin if enterococci or methicillin-resistant Staphylococcus aureus (MRSA) were among the pathogens isolated or if patients had a history of MRSA infection and additional therapy was indicated in the opinion of the investigator. Two hundred and four (204) patients randomized to ertapenem and 202 patients randomized to piperacillin/tazobactam were clinically evaluable. The clinical success rates at 10 days posttherapy were 75.0% (153/204) for ertapenem and 70.8% (143/202) for piperacillin/tazobactam.

Community Acquired Pneumonia

Ertapenem was evaluated in adults for the treatment of community acquired pneumonia in two randomized, double-blind, non-inferiority clinical trials. Both trials compared ertapenem (1 g parenterally once a day) with ceftriaxone (1 g parenterally once a day) and enrolled a total of 866 patients. Both regimens allowed the option to switch to oral amoxicillin/clavulanate for a total of 10 to 14 days of treatment (parenteral and oral). In the first trial the primary efficacy parameter was the clinical success rate in the clinically evaluable population and success rates were 92.3% (168/182) for ertapenem and 91.0% (183/201) for ceftriaxone at 7 to 14 days posttherapy (test-of-cure). In the second trial the primary efficacy parameter was the clinical success rate in the microbiologically evaluable population and success rates were 91% (91/100) for ertapenem and 91.8% (45/49) for ceftriaxone at 7 to 14 days posttherapy (test-of-cure).

Complicated Urinary Tract Infections Including Pyelonephritis

Ertapenem was evaluated in adults for the treatment of complicated urinary tract infections including pyelonephritis in two randomized, double-blind, non-inferiority clinical trials. Both trials compared ertapenem (1 g parenterally once a day) with ceftriaxone (1 g parenterally once a day) and enrolled a total of 850 patients. Both regimens allowed the option to switch to oral ciprofloxacin (500 mg twice daily) for a total of 10 to 14 days of treatment (parenteral and oral). The microbiological success rates (combined trials) at 5 to 9 days posttherapy (test-of-cure) were 89.5% (229/256) for ertapenem and 91.1% (204/224) for ceftriaxone.

Acute Pelvic Infections Including Endomyometritis, Septic Abortion and Post-Surgical Gynecological Infections

Ertapenem was evaluated in adults for the treatment of acute pelvic infections in a randomized, double-blind, non-inferiority clinical trial. This trial compared ertapenem (1 g intravenously once a day) with piperacillin/tazobactam (3.375 g intravenously every 6 hours) for 3 to 10 days and enrolled 412 patients including 350 patients with obstetric/postpartum infections and 45 patients with septic abortion. The clinical success rates in the clinically evaluable population at 2 to 4 weeks posttherapy (test-of-cure) were 93.9% (153/163) for ertapenem and 91.5% (140/153) for piperacillin/tazobactam.

Prophylaxis of Surgical Site Infections Following Elective Colorectal Surgery

Ertapenem was evaluated in adults for prophylaxis of surgical site infection following elective colorectal surgery in a multicenter, randomized, double-blind, non-inferiority clinical trial. This trial compared a single intravenous dose of ertapenem (1 g) versus cefotetan (2 g) administered over 30 minutes, 1 hour before elective colorectal surgery. Test-of-prophylaxis was defined as no evidence of surgical site infection, post-operative anastomotic leak, or unexplained antibiotic use in the clinically evaluable population up to and including at the 4-week posttreatment follow-up visit. The trial included 500 patients randomized to ertapenem and 502 patients randomized to cefotetan. The modified intent-to-treat (MITT) population consisted of 451 ertapenem patients and 450 cefotetan patients and included all patients who were randomized, treated, and underwent elective colorectal surgery with adequate bowel preparation. The clinically evaluable population was a subset of the MITT population and consisted of patients who received a complete dose of study therapy no more than two hours prior to surgical incision and no more than six hours before surgical closure. Clinically evaluable patients had sufficient information to determine outcome at the 4-week follow-up assessment and had no confounding factors that interfered with the assessment of that outcome. Examples of confounding factors included prior or concomitant antibiotic violations, the need for a second surgical procedure during the study period, and identification of a distant site infection with concomitant antibiotic administration and no evidence of subsequent wound infection. Three-hundred forty-six (346) patients randomized to ertapenem and 339 patients randomized to cefotetan were clinically evaluable. The prophylactic success rates at 4 weeks posttreatment in the clinically evaluable population were 70.5% (244/346) for ertapenem and 57.2% (194/339) for cefotetan (difference 13.3%, [95% C.I.: 6.1, 20.4], p<0.001). Prophylaxis failure due to surgical site infections occurred in 18.2% (63/346) ertapenem patients and 31.0% (105/339) cefotetan patients. Post-operative anastomotic leak occurred in 2.9% (10/346) ertapenem patients and 4.1% (14/339) cefotetan patients. Unexplained antibiotic use occurred in 8.4% (29/346) ertapenem patients and 7.7% (26/339) cefotetan patients. Though patient numbers were small in some subgroups, in general, clinical response rates by age, gender, and race were consistent with the results found in the clinically evaluable population. In the MITT analysis, the prophylactic success rates at 4 weeks posttreatment were 58.3% (263/451) for ertapenem and 48.9% (220/450) for cefotetan (difference 9.4%, [95% C.I.: 2.9, 15.9], p=0.002). A statistically significant difference favoring ertapenem over cefotetan with respect to the primary endpoint has been observed at a significance level of 5% in this trial. A second adequate and well-controlled trial to confirm these findings has not been conducted; therefore, the clinical superiority of ertapenem over cefotetan has not been demonstrated.

14.2 Pediatric Patients

Ertapenem was evaluated in pediatric patients 3 months to 17 years of age in two randomized, multicenter clinical trials.

The first trial enrolled 404 patients and compared ertapenem (15 mg/kg intravenous (IV) every 12 hours in patients 3 months to 12 years of age, and 1 g IV once a day in patients 13 to 17 years of age) to ceftriaxone (50 mg/kg/day IV in two divided doses in patients 3 months to 12 years of age and 50 mg/kg/day IV as a single daily dose in patients 13 to 17 years of age) for the treatment of complicated urinary tract infection (UTI), skin and soft tissue infection (SSTI), or community-acquired pneumonia (CAP). Both regimens allowed the option to switch to oral amoxicillin/clavulanate for a total of up to 14 days of treatment (parenteral and oral). The microbiological success rates in the evaluable per protocol (EPP) analysis in patients treated for UTI were 87.0% (40/46) for ertapenem and 90.0% (18/20) for ceftriaxone. The clinical success rates in the EPP analysis in patients treated for SSTI were 95.5% (64/67) for ertapenem and 100% (26/26) for ceftriaxone, and in patients treated for CAP were 96.1% (74/77) for ertapenem and 96.4% (27/28) for ceftriaxone.

The second trial enrolled 112 patients and compared ertapenem (15 mg/kg IV every 12 hours in patients 3 months to 12 years of age, and 1 g IV once a day in patients 13 to 17 years of age) to ticarcillin/clavulanate (50 mg/kg for patients <60 kg or 3.0 g for patients >60 kg, 4 or 6 times a day) up to 14 days for the treatment of complicated intra-abdominal infections (IAI) and acute pelvic infections (API). In patients treated for IAI (primarily patients with perforated or complicated appendicitis), the clinical success rates were 83.7% (36/43) for ertapenem and 63.6% (7/11) for ticarcillin/clavulanate in the EPP analysis. In patients treated for API (post-operative or spontaneous obstetrical endomyometritis, or septic abortion), the clinical success rates were 100% (23/23) for ertapenem and 100% (4/4) for ticarcillin/clavulanate in the EPP analysis.

16 HOW SUPPLIED/STORAGE AND HANDLING

16.1 How Supplied

Ertapenem for injection is supplied as a sterile lyophilized powder in single-dose vials containing ertapenem for intravenous infusion or for intramuscular injection as follows:

NDC 42023-221-85 in packages of 10 vials.

16.2 Storage and Handling

Before reconstitution

Do not store lyophilized powder above 25°C (77°F).

Reconstituted and infusion solutions

The reconstituted solution, immediately diluted in 0.9% Sodium Chloride Injection [see Dosage and Administration (2.7)], may be stored at room temperature (25°C) and used within 6 hours or stored for 24 hours under refrigeration (5°C) and used within 4 hours after removal from refrigeration. Solutions of ertapenem for injection should not be frozen.

17 PATIENT COUNSELING INFORMATION

17.1 Instructions for Patients

Patients should be advised that allergic reactions, including serious allergic reactions could occur and that serious reactions may require immediate treatment. Advise patients to report any previous hypersensitivity reactions to ertapenem for injection, other beta-lactams or other allergens.

Patients should be counseled to inform their physician if they are taking valproic acid or divalproex sodium. Valproic acid concentrations in the blood may drop below the therapeutic range upon co-administration with ertapenem for injection. If treatment with ertapenem for injection is necessary and continued, alternative or supplemental anti-convulsant medication to prevent and/or treat seizures may be needed.

Patients should be counseled that antibacterial drugs including ertapenem for injection should only be used to treat bacterial infections. They do not treat viral infections (e.g., the common cold). When ertapenem for injection is prescribed to treat a bacterial infection, patients should be told that although it is common to feel better early in the course of therapy, the medication should be taken exactly as directed. Skipping doses or not completing the full course of therapy may (1) decrease the effectiveness of the immediate treatment and (2) increase the likelihood that bacteria will develop resistance and will not be treatable by ertapenem for injection or other antibacterial drugs in the future.

Diarrhea is a common problem caused by antibiotics which usually ends when the antibiotic is discontinued. Sometimes after starting treatment with antibiotics, patients can develop watery and bloody stools (with or without stomach cramps and fever) even as late as two or more months after having taken the last dose of the antibiotic. If this occurs, patients should contact their physician as soon as possible.

Manufactured for: Endo USA, Malvern, PA 19355

PREMIERProRx® is a registered trademark of Premier Healthcare Alliance, L.P., used under license.

uspi-mk0826-i-2406r008-plprem

R06/2024

OS221P-01-95-09

PRINCIPAL DISPLAY PANEL - 1 g Vial Carton

NDC 42023-221-85

Ertapenem
Sodium IV/IM

FOR INTRAVENOUS OR
INTRAMUSCULAR USE

1 g

Rx only

10 Single-dose vials

Each vial contains 1 gram ertapenem,
equivalent to 1.046 grams ertapenem sodium.